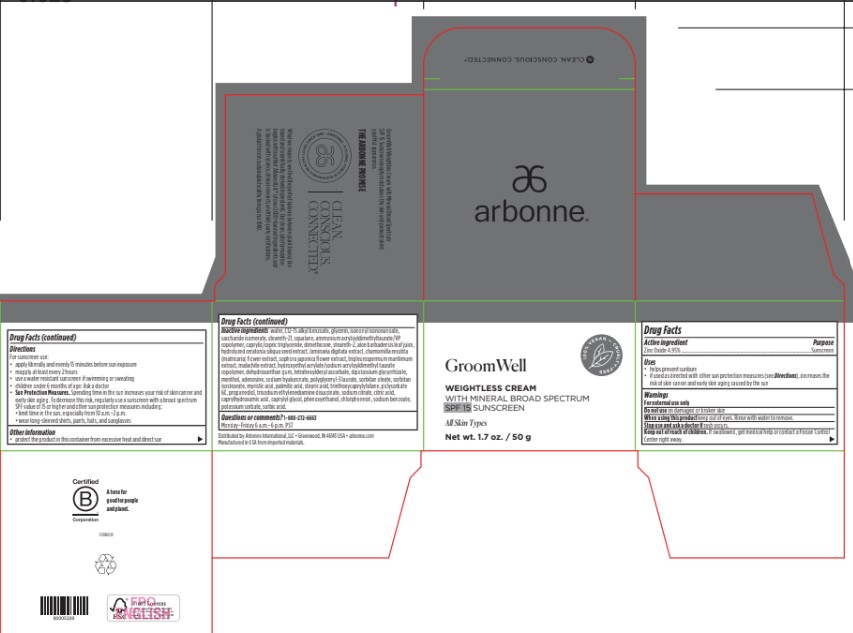 DRUG LABEL: GroomWell Weightless with Mineral Broad Spectrum SPF 15 Sunscreen
NDC: 42508-827 | Form: CREAM
Manufacturer: Arbonne International, LLC
Category: otc | Type: HUMAN OTC DRUG LABEL
Date: 20241112

ACTIVE INGREDIENTS: ZINC OXIDE 49.5 mg/1 g
INACTIVE INGREDIENTS: WATER; ALKYL (C12-15) BENZOATE; GLYCERIN; ISONONYL ISONONANOATE; SACCHARIDE ISOMERATE; STEARETH-21; SQUALANE; AMMONIUM ACRYLOYLDIMETHYLTAURATE/VP COPOLYMER; MEDIUM-CHAIN TRIGLYCERIDES; DIMETHICONE; STEARETH-2; ALOE VERA LEAF; LAMINARIA DIGITATA; CHAMOMILE; STYPHNOLOBIUM JAPONICUM FLOWER; HYDROXYETHYL ACRYLATE/SODIUM ACRYLOYLDIMETHYL TAURATE COPOLYMER (100000 MPA.S AT 1.5%); DEHYDROXANTHAN GUM; TETRAHEXYLDECYL ASCORBATE; GLYCYRRHIZINATE DIPOTASSIUM; MENTHOL, UNSPECIFIED FORM; ADENOSINE; HYALURONATE SODIUM; POLYGLYCERYL-3 LAURATE; SORBITAN MONOOLEATE; SORBITAN ISOSTEARATE; MYRISTIC ACID; PALMITIC ACID; STEARIC ACID; TRIETHOXYCAPRYLYLSILANE; POLYSORBATE 60; PROPANEDIOL; TRISODIUM ETHYLENEDIAMINE DISUCCINATE; TRISODIUM CITRATE DIHYDRATE; ANHYDROUS CITRIC ACID; CAPRYLHYDROXAMIC ACID; CAPRYLYL GLYCOL; PHENOXYETHANOL; CHLORPHENESIN; SODIUM BENZOATE; POTASSIUM SORBATE; SORBIC ACID

GroomWell Weightless with Mineral Broad Spectrum SPF 15 Sunscreen

Drug Facts

Active ingredient

Zinc Oxide 4.95%

Purpose

Sunscreen

Uses

- helps prevent sunburn
- if used as directed with other sun protection measures (see Directions), decreases the risk of skin cancer and early skin aging caused by the sun

Warnings

For external use only

Do not useon damaged or broken skin

WHEN USING

When using this productkeep out of eyes. Rinse with water to remove.

Stop use and ask a doctor ifrash occurs.

Keep out of reach of children.If swallowed, get medical help or contact a Poison Control Center right away.

Directions

For sunscreen use:

- apply liberally and evenly 15 minutes before sun exposure
- reapply at least every 2 hours
- use a water resistant sunscreen if swimming or sweating
- children under 6 months of age: Ask a doctor
- Sun Protection Measures.Spending time in the sun increases your risk of skin cancer and early skin aging. To decrease this risk, regularly use a sunscreen with a broad spectrum SPF value of 15 or higher and other sun protection measures including:
  - limit time in the sun, especially from 10 a.m.–2 p.m.
  - wear long-sleeved shirts, pants, hats, and sunglasses

Other information

- protect the product in this container from excessive heat and direct sun

Inactive ingredients

water, C12-15 alkyl benzoate, glycerin, isononyl isononanoate, saccharide isomerate, steareth-21, squalane, ammonium acryloyldimethyltaurate/VP copolymer, caprylic/capric triglyceride, dimethicone, steareth-2, aloe barbadensis leaf juice, hydrolyzed ceratonia siliqua seed extract, laminaria digitata extract, chamomilla recutita (matricaria) flower extract, sophora japonica flower extract, tripleurospermum maritimum extract, malachite extract, hydroxyethyl acrylate/sodium acryloyldimethyl taurate copolymer, dehydroxanthan gum, tetrahexyldecyl ascorbate, dipotassium glycyrrhizate, menthol, adenosine, sodium hyaluronate, polyglyceryl-3 laurate, sorbitan oleate, sorbitan isostearate, myristic acid, palmitic acid, stearic acid, triethoxycaprylylsilane, polysorbate 60, propanediol, trisodium ethylenediamine disuccinate, sodium citrate, citric acid, caprylhydroxamic acid, caprylyl glycol, phenoxyethanol, chlorphenesin, sodium benzoate, potassium sorbate, sorbic acid.

Questions or comments?

1-800-272-6663

Monday–Friday 6 a.m.–6 p.m. PST

Distributed by Arbonne International, LLC • Greenwood, IN 46143 USA

PRINCIPAL DISPLAY PANEL - 50 g Jar Carton

GroomWell

100% VEGAN – CRUELTY-FREE

WEIGHTLESS CREAM
WITH MINERAL BROAD SPECTRUM
SPF 15 SUNSCREEN

All Skin Types

Net wt. 1.7 oz. / 50 g